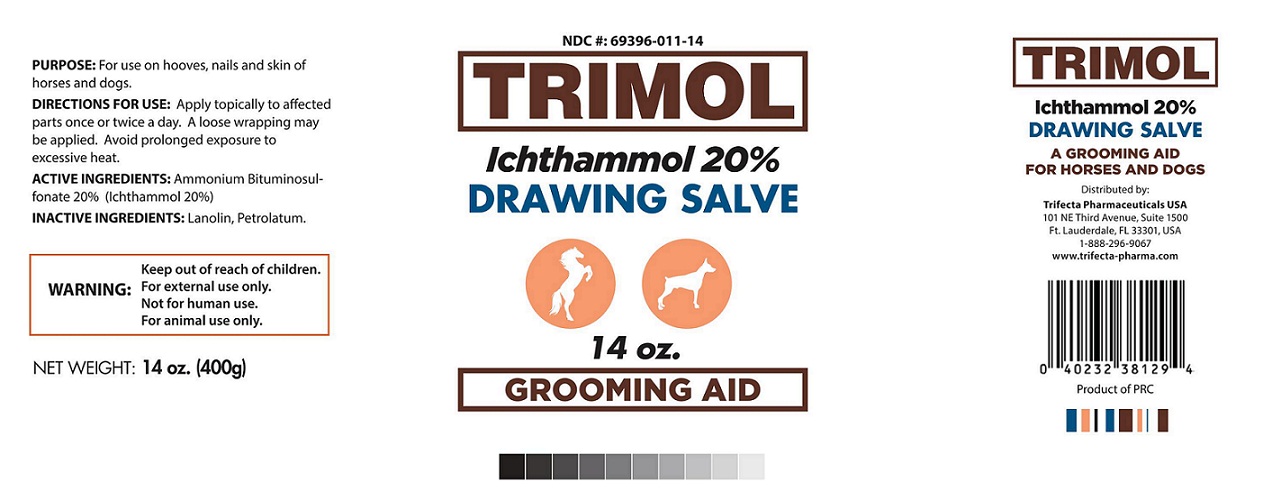 DRUG LABEL: TRIMOL Ichthammol 20%
NDC: 69396-011 | Form: OINTMENT
Manufacturer: Trifecta Pharmaceuticals Usa Llc
Category: animal | Type: OTC ANIMAL DRUG LABEL
Date: 20160225

ACTIVE INGREDIENTS: ICHTHAMMOL 20 g/100 g
INACTIVE INGREDIENTS: LANOLIN; PETROLATUM

TRIMOL Ichthammol 20% DRAWING SALVE

ACTIVE INGREDIENTS: Ammonium Bituminosulfonate 20% (Ichthammol 20%)

PURPOSE

PURPOSE: For use on hooves, nails and skin of horses and dogs

WARNING:

For external use only.

Not for human use.

For animal use only.

DOSAGE AND ADMINISTRATION

DIRECTIONS FOR USE: Apply topically to affected parts once or twice a day. A loose wrapping may be applied. Avoid prolonged exposure to excessive heat.

INACTIVE INGREDIENTS: Lanolin, Petrolatum.

A GROOMING AID FOR HORSES AND DOGS

Distributed by:

Trifecta Pharmaceuticals USA
101 NE Third Avenue, Suite 1500
Ft. Lauderdale, FL 33301, USA
1-888-296-9067
www.trifecta-pharma.com